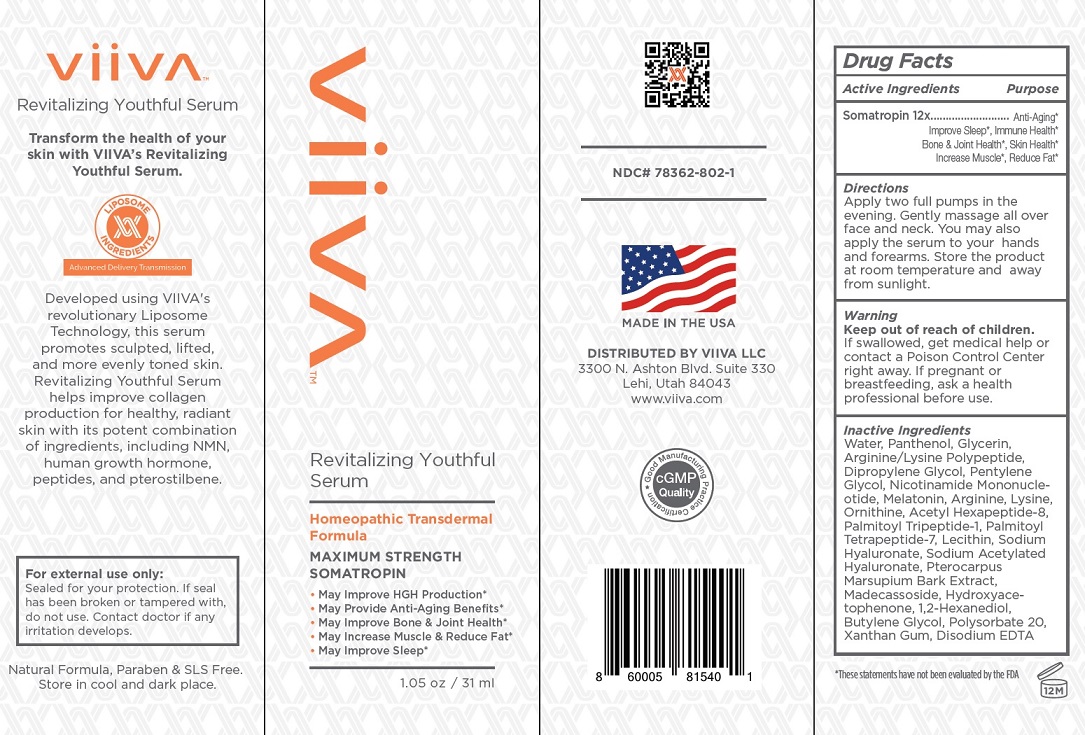 DRUG LABEL: Viiva
NDC: 78362-802 | Form: GEL
Manufacturer: Viiva LLC
Category: homeopathic | Type: HUMAN OTC DRUG LABEL
Date: 20201120

ACTIVE INGREDIENTS: SOMATROPIN 12 [hp_X]/1 mL
INACTIVE INGREDIENTS: WATER; PANTHENOL; GLYCERIN; ARGININE; DIPROPYLENE GLYCOL; PENTYLENE GLYCOL; NIACINAMIDE; MELATONIN; LYSINE; ORNITHINE; ACETYL HEXAPEPTIDE-8; PALMITOYL TRIPEPTIDE-1; PALMITOYL TETRAPEPTIDE-7; LECITHIN, SOYBEAN; HYALURONATE SODIUM; SODIUM ACETYLATED HYALURONATE; PTEROCARPUS MARSUPIUM BARK; MADECASSOSIDE; HYDROXYACETOPHENONE; 1,2-HEXANEDIOL; BUTYLENE GLYCOL; POLYSORBATE 20; XANTHAN GUM; EDETATE DISODIUM ANHYDROUS

Active Ingredients

Somatropin 12X

Purpose

Anti-Aging', Improve Sleep', Immune Health', Bone & Joint Health', Skin Health', Increase Muscle', Reduce Fat'

'These statement have not been evaluted by FDA

Directions

Apply two full pumps in the evening. Gently massage all over face and neck. You may also apply the serum to your hands and forearms. Store the product at room temperature and away from sunlight.

Warning

Keep out of reach of children.
If swallowed, get medical help or contact a Poison Control Center right away. If pregnant or breastfeeding, ask a health professional before use.

Inactive Ingredients

Water, Panthenol, Glycerin, Arginine/Lysine Polypeptide, Dipropylene Glycol, Pentylene Glycol, Nicotinamide Mononucleotide, Melatonin, Arginine, Lysine, Ornithine, Acetyl Hexapeptide-8, Palmitoyl Tripeptide-1, Palmitoyl Tetrapeptide-7, Lecithin, Sodium Hyaluronate, Sodium Acetylated
Hyaluronate, Pterocarpus Marsupium Bark Extract, Madecassoside, Hydroxyacetophenone, 1,2-Hexanediol, Butylene Glycol, Polysorbate 20,
Xanthan Gum, Disodium EDTA